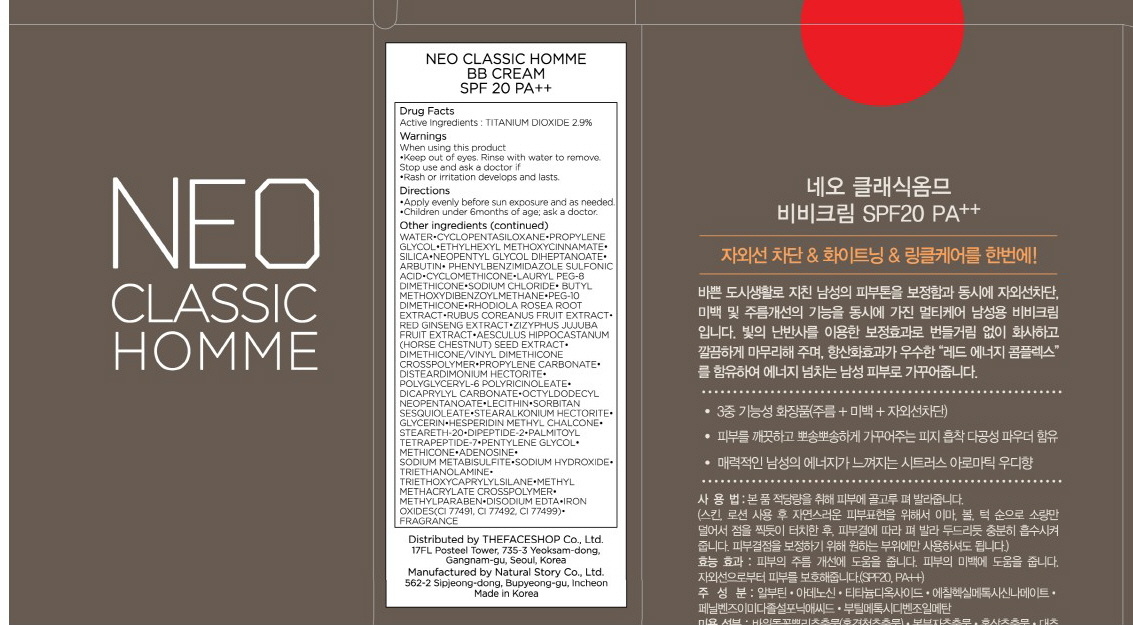 DRUG LABEL: NEO CLASSIC HOMME BB
NDC: 51523-019 | Form: CREAM
Manufacturer: THEFACESHOP CO., LTD.
Category: otc | Type: HUMAN OTC DRUG LABEL
Date: 20100714

ACTIVE INGREDIENTS: TITANIUM DIOXIDE 1.45 mL/50 mL

Drug Facts

Active Ingredient: TITANIUM DIOXIDE

Inactive Ingredients:
WATER, CYCLOPENTASILOXANE, PROPYLENE GLYCOL, ETHYLHEXYL METHOXYCINNAMATE, SILICA, NEOPENTYL GLYCOL DIHEPTANOATE, ARBUTIN, PHENYLBENZIMIDAZOLE SULFONIC ACID, CYCLOMETHICONE, LAURYL PEG-8 DIMETHICONE, SODIUM CHLORIDE, BUTYL METHOXYDIBENZOYLMETHANE, PEG-10 DIMETHICONE, RHODIOLA ROSEA ROOT EXTRACT, RUBUS COREANUS FRUIT EXTRACT, RED GINSENG EXTRACT, ZIZYPHUS, JUJUBA FRUIT EXTRACT, AESCULUS HIPPOCASTANUM (HORSE CHESTNUT) SEED EXTRACT, DIMETHICONE/VINYL DIMETHICONE CROSSPOLYMER, PROPYLENE CARBONATE, DISTEARDIMONIUM HECTORITE, POLYGLYCERYL-6 POLYRICINOLEATE, DICAPRYLYL CARBONATE, OCTYLDODECYL NEOPENTANOATE, LECITHIN, SORBITAN SESQUIOLEATE, STEARALKONIUM HECTORITE, GLYCERIN, HESPERIDIN METHYL CHALCONE, STEARETH-20, DIPEPTIDE-2, PALMITOYL TETRAPEPTIDE-7, PENTYLENE GLYCOL, METHICONE, ADENOSINE, SODIUM METABISULFITE, SODIUM HYDROXIDE, TRIETHANOLAMINE, TRIETHOXYCAPRYLYLSILANE, METHYL METHACRYLATE CROSSPOLYMER, METHYLPARABEN, DISODIUM EDTA, IRON OXIDES(CI 77491, CI 77492, CI 77499), FRAGRANCE

Warnings:
When using this product
Keep out of eyes. Rinse with water to remove.
Stop use and ask a doctor if
Rash or irritation develops and lasts.
Directions:
Apply evenly before sun exposure and as needed.
Children under 6months of age; ask a doctor.